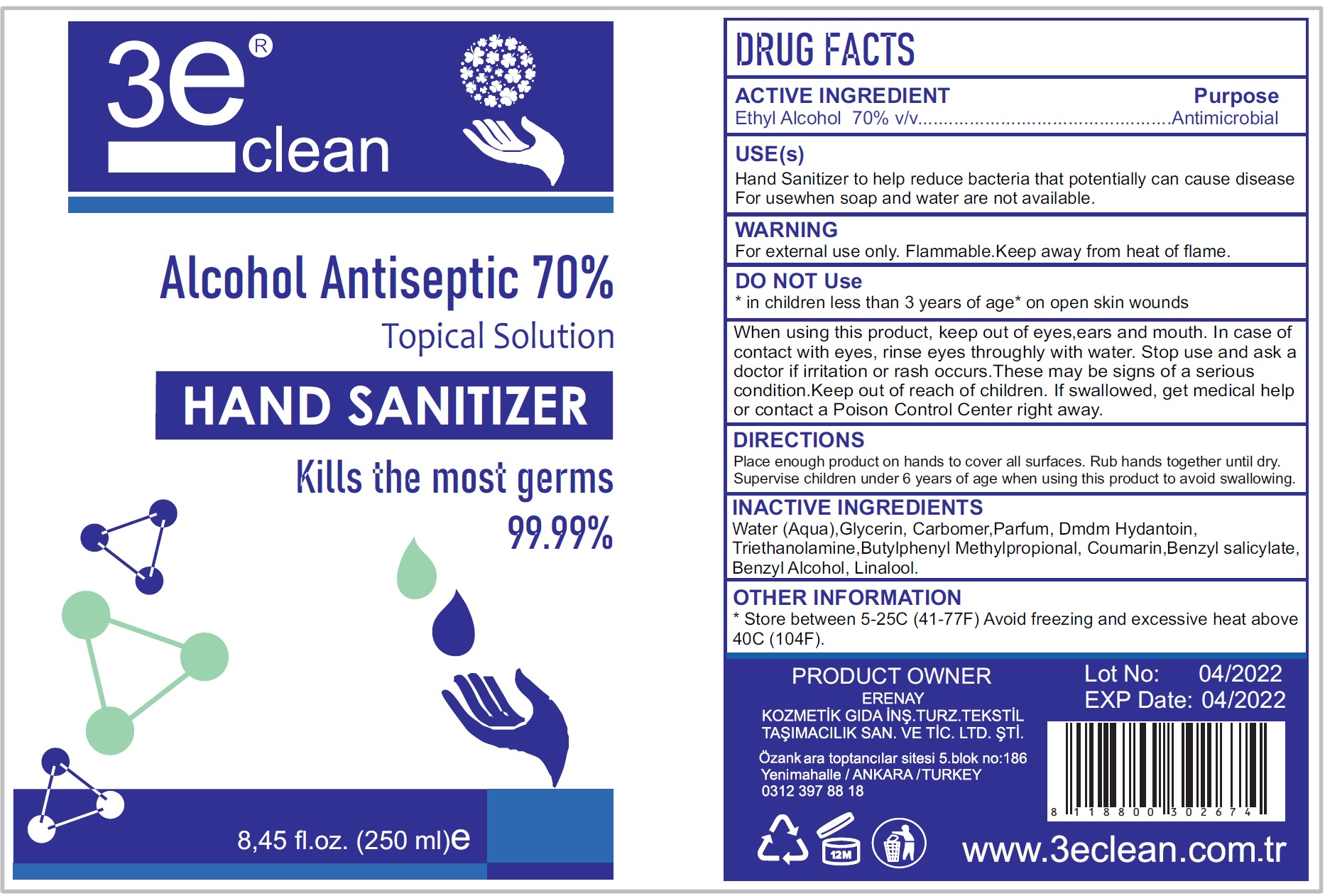 DRUG LABEL: 3e Clean Hand Sanitizer
NDC: 78896-001 | Form: LIQUID
Manufacturer: Erenay Kozmetik Gida Insaat Turizm Tekstil Tasimacilik Sanayi LTD. STI.
Category: otc | Type: HUMAN OTC DRUG LABEL
Date: 20200619

ACTIVE INGREDIENTS: ALCOHOL 0.7 mL/1 mL
INACTIVE INGREDIENTS: WATER; GLYCERIN; CARBOMER HOMOPOLYMER, UNSPECIFIED TYPE; DMDM HYDANTOIN; TROLAMINE; BUTYLPHENYL METHYLPROPIONAL; COUMARIN; BENZYL SALICYLATE; BENZYL ALCOHOL; LINALOOL, (+/-)-

3e Clean Hand Sanitizer

ACTIVE INGREDIENT

Ethyl Alcohol 70% v/v

Purpose

Antimicrobial

USE(s)

Hand Sanitizer to help reduce bacteria that potentially can cause disease For usewhen soap and water are not available.

WARNING

For external use only. Flammable.Keep away from heat of flame.

DO NOT Use

* in children less than 3 years of age* on open skin wounds

When using this product,

keep out of eyes,ears and mouth. In case of contact with eyes, rinse eyes throughly with water.

Stop use and ask a doctor

if irritation or rash occurs.These may be signs of a serious condition.

Keep out of reach of children.

If swallowed, get medical help or contact a Poison Control Center right away.

DIRECTIONS

Place enough product on hands to cover all surfaces. Rub hands together until dry. Supervise children under 6 years of age when using this product to avoid swallowing.

INACTIVE INGREDIENTS

Water (Aqua),Glycerin, Carbomer,Parfum, Dmdm Hydantoin, Triethanolamine,Butylphenyl Methylpropional, Coumarin,Benzyl salicylate, Benzyl Alcohol, Linalool.

OTHER INFORMATION

* Store between 5-25C (41-77F) Avoid freezing and excessive heat above 40C (104F).